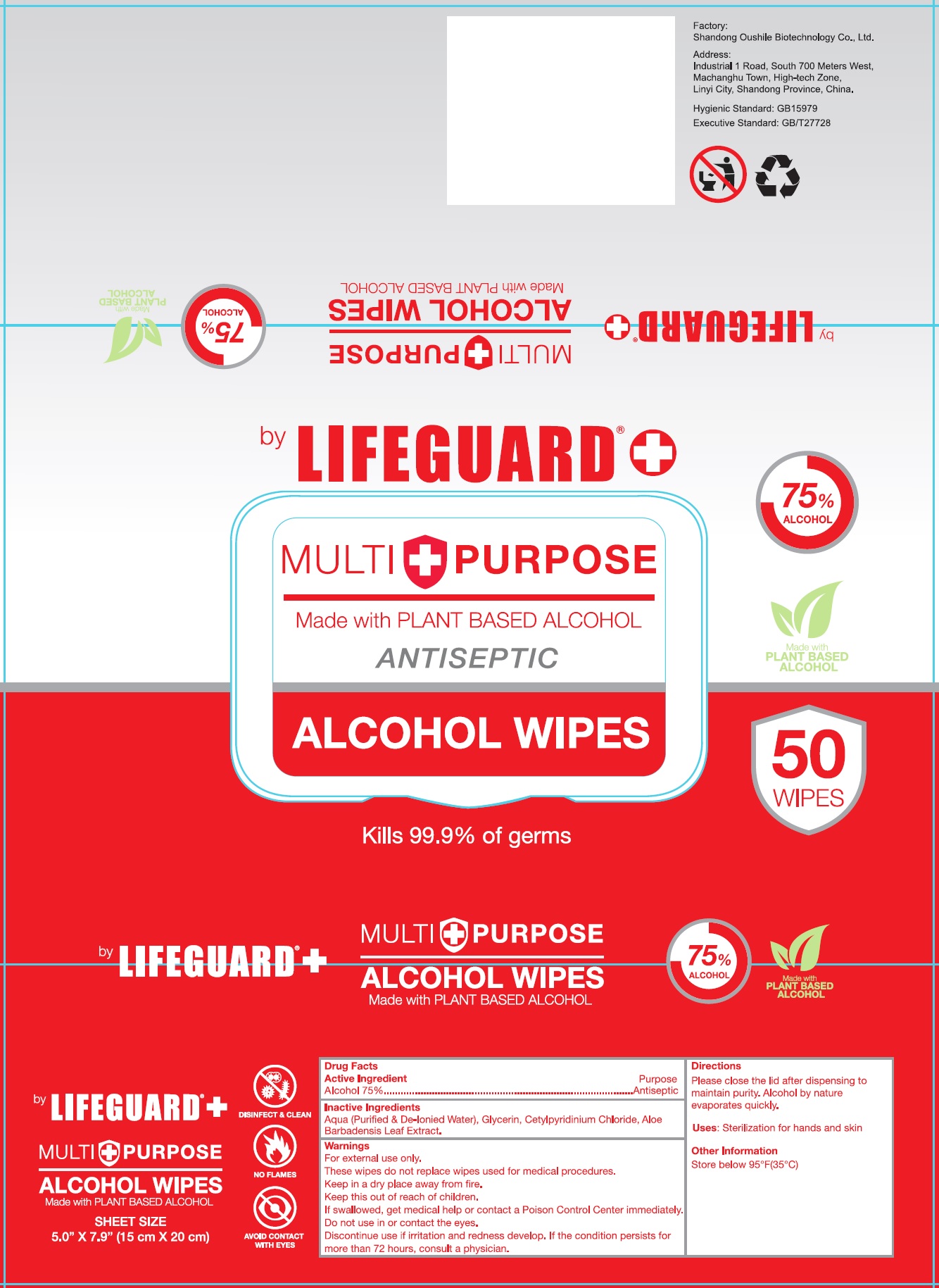 DRUG LABEL: LIFEGUARD Multipurpose Antiseptic Alcohol Wipes
NDC: 77879-003 | Form: CLOTH
Manufacturer: BT Supplies West Inc
Category: otc | Type: HUMAN OTC DRUG LABEL
Date: 20201015

ACTIVE INGREDIENTS: ALCOHOL 0.75 mL/1 mL
INACTIVE INGREDIENTS: WATER; GLYCERIN; CETYLPYRIDINIUM CHLORIDE; ALOE VERA LEAF

LIFEGUARD Multipurpose Antiseptic Alcohol Wipes

Active Ingredient

Alcohol 75%

Purpose

Antiseptic

Inactive Ingredients

Aqua (Purified & De-Ionied Water), Glycerin, Cetylpyridinium Chloride, Aloe Barbadensis Leaf Extract.

Warnings

For external use only.

These wipes do not replace wipes used for medical procedures.

Keep in a dry place away from fire.

Keep this out of reach of children.

If swallowed, get medical help or contact a Poison Control Center immediately.

Do not use

in or contact the eyes.

Discontinue use if irritation and redness develop. If the condition persists for more than 72 hours, consult a physician.

Directions

Please close the lid after dispensing to maintain purity. Alcohol by nature evaporates quickly.

Uses:

Sterillization for hands and skin

Other Information

Store below 95°F(35°C)